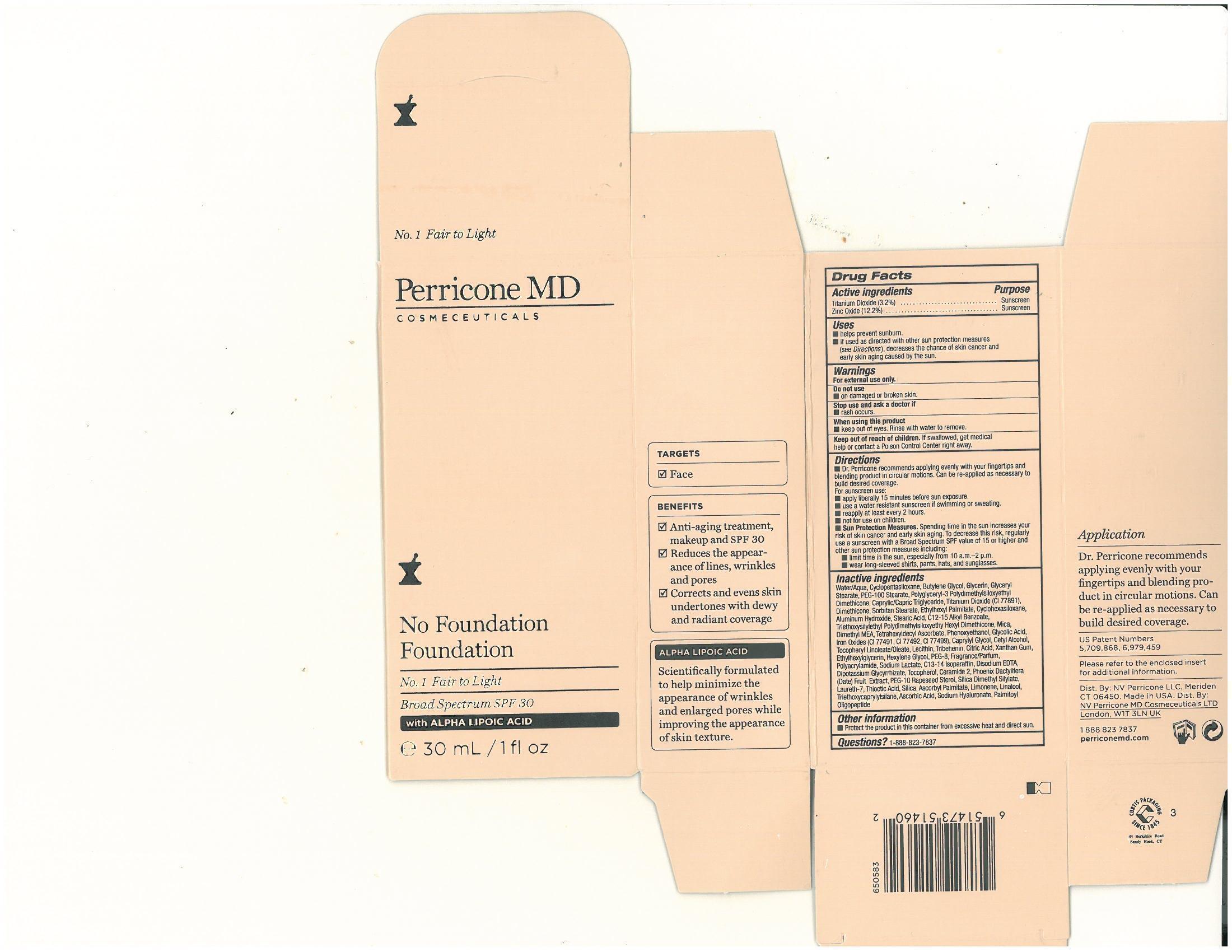 DRUG LABEL: No Foundation Foundation No.1 Fair to Light
NDC: 62742-4063 | Form: CREAM
Manufacturer: Allure Labs, Inc
Category: otc | Type: HUMAN OTC DRUG LABEL
Date: 20140418

ACTIVE INGREDIENTS: ZINC OXIDE 122 mg/1 mL; TITANIUM DIOXIDE 32 mg/1 mL
INACTIVE INGREDIENTS: WATER; CYCLOMETHICONE 5; BUTYLENE GLYCOL; GLYCERIN ; GLYCERYL MONOSTEARATE; PEG-100 STEARATE; MEDIUM-CHAIN TRIGLYCERIDES; DIMETHICONE; SORBITAN MONOSTEARATE; ETHYLHEXYL PALMITATE; CYCLOMETHICONE 6; Aluminum Hydroxide; STEARIC ACID ; C12-15 Alkyl Benzoate; MICA; DEANOL; TETRAHEXYLDECYL ASCORBATE ; PHENOXYETHANOL ; GLYCOLIC ACID ; FERRIC OXIDE RED ; FERRIC OXIDE YELLOW; FERROSOFERRIC OXIDE; Caprylyl Glycol ; CETYL ALCOHOL; .ALPHA.-TOCOPHEROL LINOLEATE, D- ; TRIBEHENIN  ; CITRIC ACID MONOHYDRATE; XANTHAN GUM; ETHYLHEXYLGLYCERIN; HEXYLENE GLYCOL; POLYETHYLENE GLYCOL 400  ; POLYACRYLAMIDE (10000 MW); SODIUM LACTATE; C13-14 ISOPARAFFIN; EDETATE DISODIUM; GLYCYRRHIZINATE DIPOTASSIUM ; TOCOPHEROL ; CERAMIDE 2; DATE; PEG-10 RAPESEED STEROL; SILICON DIOXIDE; LAURETH-7; .ALPHA.-LIPOIC ACID; ASCORBYL PALMITATE; LIMONENE, (+)-; LINALOOL, (+/-)-; TRIETHOXYCAPRYLYLSILANE ; ASCORBIC ACID; HYALURONATE SODIUM; PALMITOYL OLIGOPEPTIDE 

DRUG FACTS

ACTIVE INGREDIENTS:
Zinc Oxide - 12.2%
Titanium Dioxide 3.2%

Purpose: Sunscreen

Uses:

Helps prevent sunburn if used as directed with other sun protection measures (see Directions) decreases the chance of skin cancer and early skin aging caused by the sun

Warnings

For External Use Only

Do not use on damaged or broken skin.

When using this product keep out of eyes. Rinse with water to remove

Stop use and ask doctor if rash ocuur

Keep out of reach of children. If swallowed, get medical help or contact a Poison Control Center right away

Directions:

- Dr. Perricone recommends applying evenly with your fingertips and blending product in circular motions. Can be re-applied as necessary to build desired coverage.
- Apply liberally 15 minutes before sun exposure.
- Use a water resistant sunscreen if swimming or sweating.
- Re apply at least every 2 hours.
- Not for use on children.
- Sun Protection Measures. Spending time in the sun increases your risk of skin cancer and early skin aging. To decrease this risk regularly use a sunscreen with a broad spectrum SPF value of 15 or higher and other sun protection measures including;
  1. Limit time in the sun, especially between 10am to 2pm
- 2. Wear long sleeved shirts, pants, hats, and sun glasses

STORAGE AND HANDLING

Protect the product in this container from excessive heat and direct sun.

INACTIVE INGREDIENT

Water/Aqua, Cyclopentasiloxane, Butylene Glycol, Glycerin, Glyceryl Stearate, PEG-100 Stearate, Polyglyceryl-3 Polydimethylsiloxyethyl Dimethicone, Caprylic/Capric Triglyceride, Titanium Dioxide (CI 77891), Dimethicone, Sorbitan Stearate, Ethylhexyl Palmitate, Cyclohexasiloxane, Aluminum Hydroxide, Stearic Acid, C12-C15 Alkyl Benzoate, Triethoxysilyethyl Polydimethylsiloxyethy Hexyl Dimethicone, Mica, Dimethyl MEA, Tetrahexyldecyl Ascorbate, Phenoxyethanol, Glycolic Acid, Iron Oxides (CI 77491, CI 77492, CI 77499) Caprylyl Glycol, Cetyl Alcohol, Tocopheryl Linoleate/Oleate, Lecithin, Tribehenin, Citric Acid, Xanthan Gum, Ethylhexylglycerin, Hexylele Glycol, PEG-8, Fragrance/Parfum, Polyacrylamide, Sodium Lactate, C13-14 Isoparaffin, Disodium EDTA, Diopotassium Glycyrrhizate, Tocopheryl, Ceramide 2, Pheonix Dactylifera (Date) Fruit Extract, PEG-10 Rapeseed Sterikm Silica Dimethyl Silylate, Laureth-7, Thiotic Acid, Silica, Ascorbyl Palmitate, Limonene, Linalool, Triethoxycaprylylsilane, Ascorbic Acid, Sodium Hyaluronate, Palmitoyl Oligopeptide

PACKAGE LABEL

Distributed By: NV Perricone LLC, Meriden CT 06450, Made in USA

NV Perricone MD Cosmeceuticals LTD, London. W1T 3LN UK

www.perriconemd.com

1 888 823 7837